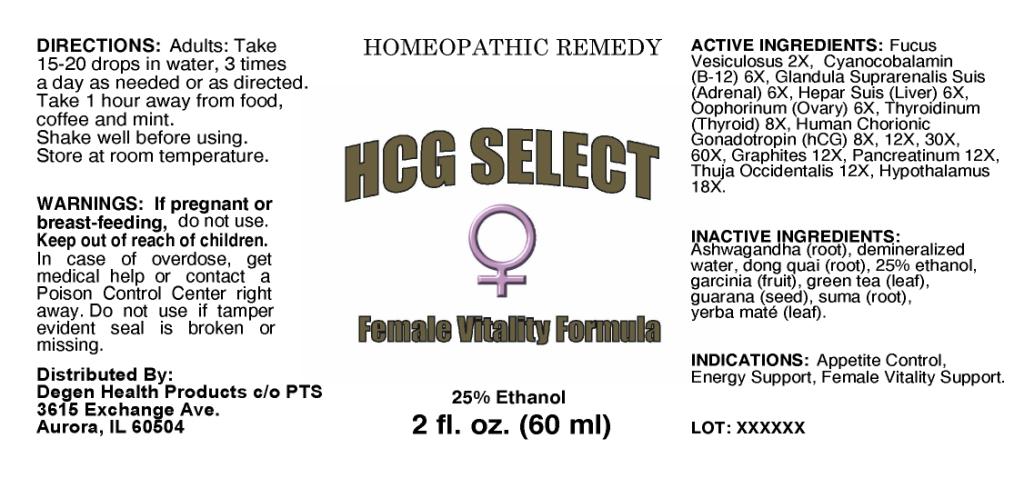 DRUG LABEL: HCG Select Female Vitality Formula
NDC: 57520-0382 | Form: LIQUID
Manufacturer: Apotheca Company
Category: homeopathic | Type: HUMAN OTC DRUG LABEL
Date: 20100901

ACTIVE INGREDIENTS: FUCUS VESICULOSUS 2 [hp_X]/1 mL; CYANOCOBALAMIN 6 [hp_X]/1 mL; SUS SCROFA ADRENAL GLAND 6 [hp_X]/1 mL; PORK LIVER 6 [hp_X]/1 mL; SUS SCROFA OVARY 6 [hp_X]/1 mL; HUMAN CHORIONIC GONADOTROPIN 60 [hp_X]/1 mL; SUS SCROFA THYROID 8 [hp_X]/1 mL; GRAPHITE 12 [hp_X]/1 mL; PANCRELIPASE 12 [hp_X]/1 mL; THUJA OCCIDENTALIS LEAFY TWIG 12 [hp_X]/1 mL; SUS SCROFA HYPOTHALAMUS 18 [hp_X]/1 mL
INACTIVE INGREDIENTS: WATER; ALCOHOL; GREEN TEA LEAF; PAULLINIA CUPANA SEED; ILEX PARAGUARIENSIS LEAF; ANGELICA SINENSIS ROOT; WITHANIA SOMNIFERA ROOT    ; GARCINIA CAMBOGIA FRUIT; PFAFFIA PANICULATA ROOT

HCG Select Female Vitality Formula

ACTIVE INGREDIENT

ACTIVE INGREDIENTS: Fucus vesiculosus 2X, Cyanocobalamin (B-12) 6X, Slandula suprarenalis suis(Adrenal) 6X, Hepar suis(Liver) 6X, Oophorinum(Ovary) 6X, Human chorionic gonadotropin (hCG) 8X, 12X, 30X, 60X, Thyroidinum(Thyroid) 8X, Graphites 12X, Pancreatinum 12X, Thuja occidentalis 12X, Hypothalamus 18X.

PURPOSE

INDICATIONS: Appetite control, Energy support, Female vitality support.

WARNINGS

WARNINGS: If pregnant or breast-feeding, do not use.

Keep out of reach of children. In case of overdose, get medical help or contact a Poison Control Center right away.

Do not use if tamper evident seal is broken or missing.

DOSAGE AND ADMINISTRATION

DIRECTIONS: Adults: Take 15-20 drops in water, 3 times a day as needed or as directed. Take 1 hour away from food, coffee and mint. Shake well before using. Store at room temperature.

INACTIVE INGREDIENT

INACTIVE INGREDIENTS: Demineralized water, 25% Ethanol, Green tea(leaf), Guarana(seed), Yerba mate(leaf), Ashwagandha(root), Dong quai(root), Garcinia(fruit), Suma(root).

KEEP OUT OF REACH OF CHILDREN: In case of overdose, get medical help or contact a Poison Control Center right away.

INDICATIONS AND USAGE

INDICATIONS: Appetite control, Energy support, Female vitality support.

QUESTIONS

Distributed By:

Degen Health Products c/o PTS

3615 Exchange Ave.

Aurora, IL 60504

PACKAGE LABEL

HOMEOPATHIC REMEDY

HCG SELECT

FEMALE VITALITY FORMULA

2 fl. oz. (60 ml)